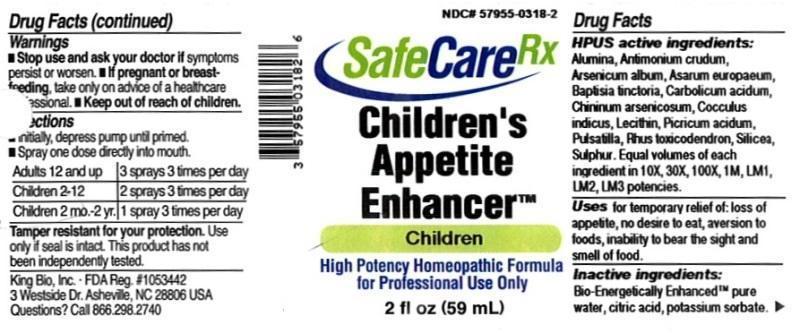 DRUG LABEL: Childrens Appetite Enhancer
NDC: 57955-0318 | Form: LIQUID
Manufacturer: King Bio Inc.
Category: homeopathic | Type: HUMAN OTC DRUG LABEL
Date: 20150831

ACTIVE INGREDIENTS: ALUMINUM OXIDE 10 [hp_X]/59 mL; ANTIMONY TRISULFIDE 10 [hp_X]/59 mL; ARSENIC TRIOXIDE 10 [hp_X]/59 mL; ASARUM EUROPAEUM 10 [hp_X]/59 mL; BAPTISIA TINCTORIA ROOT 10 [hp_X]/59 mL; PHENOL 10 [hp_X]/59 mL; QUININE ARSENITE 10 [hp_X]/59 mL; ANAMIRTA COCCULUS SEED 10 [hp_X]/59 mL; EGG PHOSPHOLIPIDS 10 [hp_X]/59 mL; PICRIC ACID 10 [hp_X]/59 mL; PULSATILLA VULGARIS 10 [hp_X]/59 mL; TOXICODENDRON PUBESCENS LEAF 10 [hp_X]/59 mL; SILICON DIOXIDE 10 [hp_X]/59 mL; SULFUR 10 [hp_X]/59 mL
INACTIVE INGREDIENTS: WATER; ANHYDROUS CITRIC ACID; POTASSIUM SORBATE

Children's Appetite Enhancer™

ACTIVE INGREDIENT

Drug Facts__________________________________________________________________________________________________________

HPUS active ingredients: Alumina, Antimonium crudum, Arsenicum album, Asarum europaeum, Baptisia tinctoria, Carbolicum acidum, Chininum arsenicosum, Cocculus indicus, Lecithin, Picricum acidum, Pulsatilla, Rhus toxicodendron, Silicea, Sulphur. Equal volumes of each ingredient in 10X, 30X, 100X, 1M, LM1, LM2, LM3 potencies.

INDICATIONS AND USAGE

Uses for temporary relief of: loss of appetite, no desire to eat, aversion to foods, inability to bear the sight and smell of food.

Inactive Ingredients:

Bio-Energetically Enhanced™ pure water, citric acid and potassium sorbate.

Warnings

- Stop use and ask your doctor if symptoms persist or worsen.
- If pregnant or breast-feeding, take only on advice of a healthcare professional.

- Keep out of reach of children.

Directions

- Initially, depress pump until primed.
- Spray one dose directly into mouth.
- Adults 12 and up: 3 sprays 3 times per day.
- Children 2-12: 2 sprays 3 times per day.
- Children 2 mo-2 yr: 1 spray 3 times per day.

OTHER SAFETY INFORMATION

Tamper resistant for your protection. Use only if safety seal is intact. This product has not been independently tested.

PURPOSE

Uses for temporary relief of:

- loss of appetite
- no desire to eat
- aversion to foods
- inability to bear the sight and smell of food